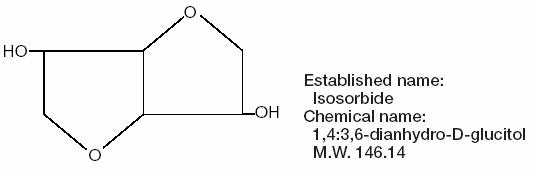 DRUG LABEL: Unknown
Manufacturer: Alcon Laboratories, Inc.
Category: prescription | Type: Human Prescription Drug Label
Date: 20060323

ISMOTIC®
(isosorbide solution)
45% w/v Solution

DESCRIPTION

ISMOTIC® is a 45% w/v solution of isosorbide in a vanilla-mint flavored vehicle. ISMOTIC is a caramel colored aqueous solution that is chemically stable at room temperature.

Each mL contains:

Isosorbide 45% w/v (Isosorbide Concentrate 60.6%), Alcohol 0.3% w/v, Caramel, Creme de Menthe, Malic Acid, Potassium Citrate, Potassium Sorbate, Saccharin Calcium, Sodium Citrate, Sorbitol Solution, Vanilla Concentrate Imitation #20, Potassium Hydroxide (to adjust pH), and Purified Water.

DM-00

Typical analysis of electrolyte content:

4.6 meq. of Sodium/220 mL ISMOTIC Solution

0.9 meq. of Potassium/220 mL ISMOTIC Solution

Isosorbide, the osmotic agent in ISMOTIC, is a dihydric alcohol with the formula C6H10O4 represented by the structure:

CLINICAL PHARMACOLOGY

Isosorbide is rapidly absorbed after oral administration. It is essentially nonmetabolized, and in the circulation, it contributes to the tonicity of the blood until it is eliminated by the kidney unchanged. While in the blood, isosorbide acts as an osmotic agent to promote redistribution of water toward the circulation with ultimate elimination in the urine. The physical action of ISMOTIC is similar to that of other osmotic drugs.

INDICATIONS AND USAGE

For the short-term reduction of intraocular pressure. May be used prior to and after intraocular surgery. May be used to interrupt an acute attack of glaucoma.

CONTRAINDICATIONS

1. Well-established anuria
2. Severe dehydration
3. Frank or impending acute pulmonary edema
4. Severe cardiac decompensation
5. Hypersensitivity to any component of this preparation

WARNINGS

1. With repeated doses, consideration should be given to maintenance of adequate fluid and electrolyte balance.
2. If urinary output continues to decrease, the patient’s clinical status should be closely reviewed. Accumulation of ISMOTIC may result in overexpansion of the extracellular fluid.

PRECAUTIONS

General

For oral use only – not for injection. Repetitive doses should be used with caution particularly in patients with diseases associated with salt retention. Ensure that patient’s bladder has been emptied prior to surgery.

Carcinogenesis, Mutagenesis, Impairment of Fertility

No studies have been conducted in animals or in humans to evaluate the potential of these effects.

Pregnancy

Pregnancy Category B

Reproduction (fertility and teratology) studies have been performed in rats at doses approximately 5 times the recommended initial human dose of 1.5 gm/kg body weight and have revealed no evidence of impaired fertility or harm to the fetus due to isosorbide. Teratology studies have been performed with rabbits and rats given daily oral doses of isosorbide at 6.5 and 10 times, respectively, the recommended initial human dose during organogenesis without evidence of harm to the fetus. There are, however, no adequate and well-controlled studies in pregnant women. Because animal studies are not always predictive of human responses, this drug should be used during pregnancy only if clearly needed.

Nursing Mothers

It is not known whether this drug is excreted in human milk. Because many drugs are excreted in breast milk, caution should be exercised when isosorbide is administered to a nursing mother.

Pediatric Use

Safety and effectiveness in pediatric patients have not been established.

ADVERSE REACTIONS

Nausea, vomiting, headache, confusion, and disorientation may occur. Occurrences of syncope, gastric discomfort, lethargy, vertigo, thirst, dizziness, hiccups, hypernatremia, hyperosmolarity, irritability, rash and light-headedness have been reported.

DOSAGE AND ADMINISTRATION

The recommended initial dose of isosorbide is 1.5 gm/kg body weight (equivalent to 1.5 mL /lb. of body weight). The onset of action is usually within 30 minutes while the maximum effect is expected at 1 to 1 1/2 hours. The useful dose range is 1 to 3 gm/kg body weight and the drug effect will persist up to 5 to 6 hours. Use two to four times a day as indicated. Palatability may be improved if the medication is poured over cracked ice and sipped.

RECOMMENDED DOSAGES ARE:

POUNDS | MILLILITERS | POUNDS | MILLILITERS
100 | 150 | 155 | 235
105 | 155 | 160 | 240
110 | 165 | 165 | 250
115 | 170 | 170 | 255
120 | 180 | 175 | 265
125 | 190 | 180 | 270
130 | 195 | 185 | 280
135 | 205 | 190 | 285
140 | 210 | 195 | 295
145 | 220 | 200 | 300
150 | 225

HOW SUPPLIED

Disposable plastic bottles of 220 mL (100 gm of isosorbide/220 mL) for oral use only.

NDC 0065-0034-08

Storage: Store at 15°-30°C (59°-86°F).

CAUTION: Federal (USA) law prohibits dispensing without prescription.

Mfd. for: Alcon Laboratories, Inc.

Fort Worth, Texas 76134 USA

Mfd. by: ALCON (Puerto Rico) INC.

Humacao, Puerto Rico 00791 USA

July 1997 Printed in USA

249165-0797